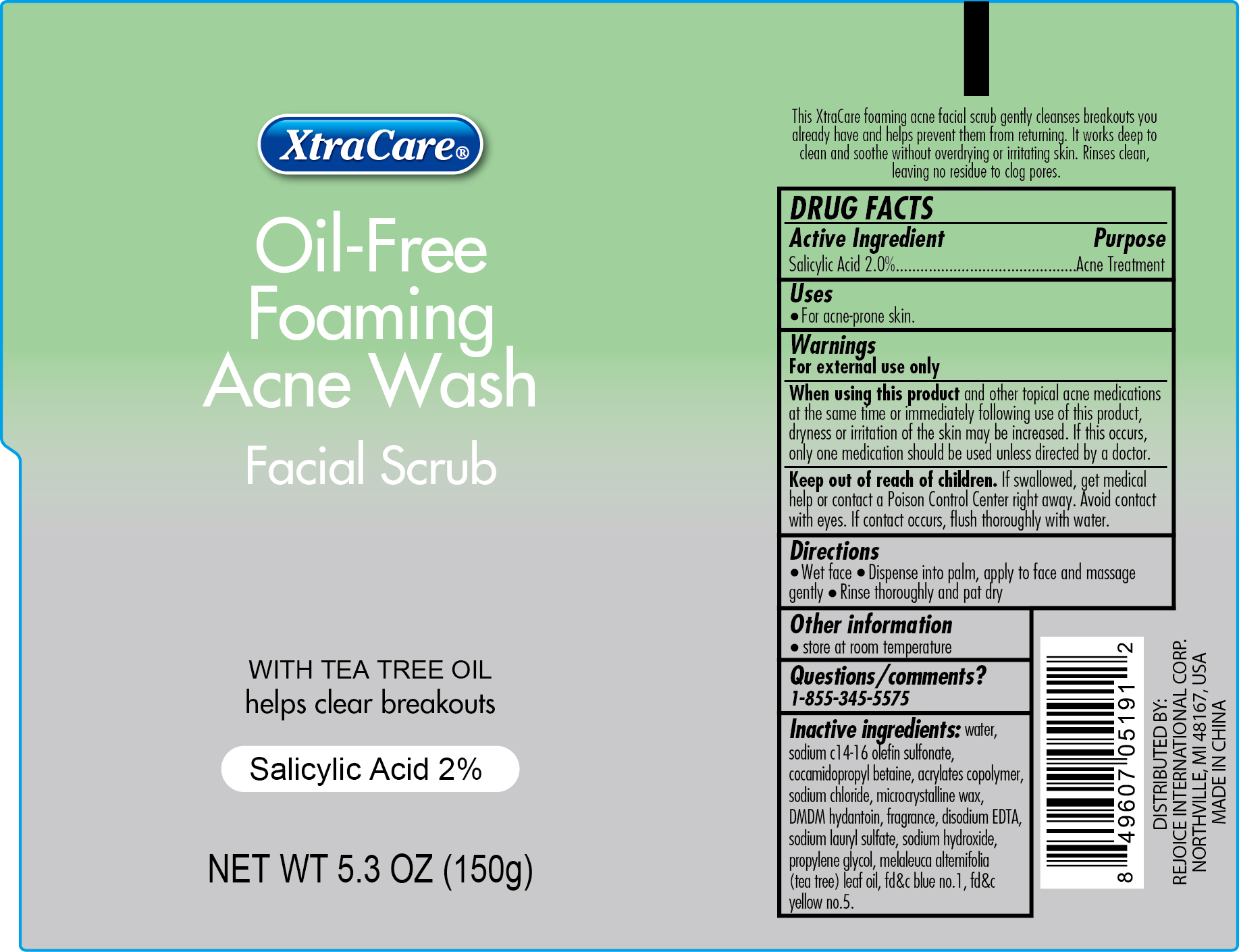 DRUG LABEL: Oil-Free Foaming Acne Wash
NDC: 57337-032 | Form: GEL
Manufacturer: Rejoice International
Category: otc | Type: HUMAN OTC DRUG LABEL
Date: 20250116

ACTIVE INGREDIENTS: SALICYLIC ACID 3 g/150 g
INACTIVE INGREDIENTS: PROPYLENE GLYCOL; BUTYL ACRYLATE/METHYL METHACRYLATE/METHACRYLIC ACID COPOLYMER (18000 MW); SODIUM CHLORIDE; MICROCRYSTALLINE WAX; DMDM HYDANTOIN; WATER; SODIUM C14-16 OLEFIN SULFONATE; COCAMIDOPROPYL BETAINE; CARBOMER COPOLYMER TYPE A (ALLYL PENTAERYTHRITOL CROSSLINKED); SODIUM LAURYL SULFATE; EDETATE DISODIUM; SODIUM HYDROXIDE; MELALEUCA ALTERNIFOLIA LEAF; FD&C BLUE NO. 1; FD&C YELLOW NO. 5

Oil-Free Foaming Acne Wash

Active Ingredient Purpose

Salicylic Acid 2.0% ................. Acne Treatment

PURPOSE

XtraCare Oil-Free Foaming Acne Wash Facial Scrub

WITH TEA TREE OIL

helps clear breakouts

Salicylic Acid 2%

Net Wt 5.3 Oz (150g)

Keep out of reach of children. If swallowed, get medical help or contact a Poison Control Center right away. Avoid contact with eyes. If contact occurs, flush thoroughly with water.

INDICATIONS AND USAGE

This XtraCare foaming acne facial scrub gently cleanses breakouts you already have and helps prevent them from returning. It works deep to clean and soothe without overdrying or irritating skin. Rinses clean, leaving no residue to clog pores.

Uses

For acne-prone skin.

Warnings

For external use only

When using this product and other topical acne medications at the same time or immediately following use of this product, dryness or irritation of the skin may be increased. If this occurs, only one medication should be used unless directed by a doctor.

Directions

Wet face. Dispense into palm, apply to face and massage gently. Rinse thoroughly and pat dry.

Other Information

store at 20o to 25oC (68o to 77oF)

DISTRIBUTED BY

REJOICE INTERNATIONAL INC

48325 BINGHAMPTON DR

NORTHVILLE, MI 48168 USA

MADE IN CHINA

Inactive ingredients

water, sodium c14-16 olefin sulfonate, cocamidopropyl betaine, acrylates copolymer, sodium chloride, microcrystalline wax, DMDM hydantoin, fragrance, disodium EDTA, sodium lauryl sulfate, sodium hydroxide, propylene glycol, melaleuca altemifolia (tea tree) leaf oil, fd&c blue no.1, fd&c yellow no.5.